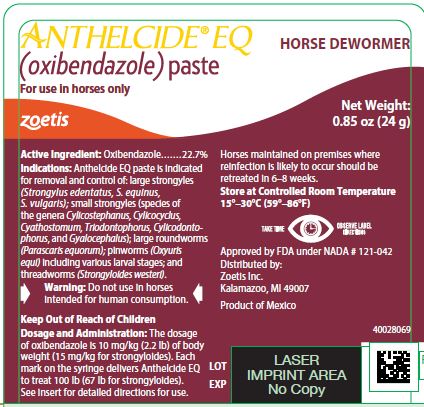 DRUG LABEL: Anthelcide EQ
NDC: 54771-6045 | Form: PASTE
Manufacturer: Zoetis Inc.
Category: animal | Type: OTC ANIMAL DRUG LABEL
Date: 20260127

ACTIVE INGREDIENTS: OXIBENDAZOLE 227 mg/1 g

ANTHELCIDE® EQ
(oxibendazole) paste

HORSE DEWORMER

For use in horses only

DESCRIPTION

Anthelcide EQ Paste is a paste formulation of oxibendazole, a broad-spectrum benzimidazole anthelmintic. This formulation has been developed for ease of administration. Each syringe contains 0.85 oz (24 g) of paste.

Anthelcide EQ Paste contains:

Oxibendazole

22.7%

INDICATIONS

Anthelcide EQ Paste is indicated for removal and control of: large strongyles (Strongylus edentatus, S. equinus, S. vulgaris); small strongyles (species of the genera Cylicostephanus, Cylicocyclus, Cyathostomum, Triodontophorus, Cylicodontophorus, and Gyalocephalus); large roundworms (Parascaris equorum); pinworms (Oxyuris equi) including various larval stages; and threadworms (Strongyloides westeri).

CONTRAINDICATIONS

Anthelcide EQ is contraindicated in severely debilitated horses or horses suffering from infectious disease, toxemia, or colic.

Warning

Do not use in horses intended for human consumption.

PRECAUTIONS

Consult your veterinarian for assistance in the diagnosis, treatment, and control of parasitism.

Keep Out of Reach of Children.

OTHER WARNINGS

Parasite resistance may develop to any dewormer, and has been reported for most classes of dewormers. Treatment with a dewormer used in conjunction with parasite management practices appropriate to the geographic area and the animal(s) to be treated may slow the development of parasite resistance. Fecal examinations or other diagnostic tests and parasite management history should be used to determine if the product is appropriate for the herd prior to the use of any dewormer. Following the use of any dewormer, effectiveness of treatment should be monitored (for example, with the use of a fecal egg count reduction test or another appropriate method). A decrease in a drug’s effectiveness over time as calculated by fecal egg count reduction tests may indicate the development of resistance to the dewormer administered. Your parasite management plan should be adjusted accordingly based on regular monitoring.

DOSAGE AND ADMINISTRATION

The dosage of oxibendazole is 10 mg/kg (2.2 lb) of body weight (15 mg/kg for strongyloides). Each mark on the syringe delivers Anthelcide EQ to treat 100 lb (67 lb for strongyloides). Horses maintained on premises where reinfection is likely to occur should be retreated in 6–8 weeks.

Do not underdose. Ensure each animal receives a complete dose based on a current body weight. Underdosing may result in ineffective treatment, and encourage the development of parasite resistance.

Dosage Table
10 mg/kg |  | 15 mg/kg
Syringe Mark | Horse Weight (lb) | Syringe Mark | Horse Weight (lb)
100 | 100 | 300 | 200
200 | 200 | 600 | 400
400 | 400 | 900 | 600
600 | 600 | 1200 | 800
800 | 800
1000 | 1000
1200 | 1200

Anthelcide EQ is compatible with carbon disulfide, which can be used concurrently for bot control (Gasterophilus spp.) when administered by a veterinarian. Routine carbon disulfide cautions must be observed.

USE OF SYRINGE

Determine the weight of the horse and dial the correct setting on the plunger, having the side of the wheel nearest the barrel on the desired mark. Remove the cap from the syringe. Insert the tip of the syringe into the side of the animal's mouth between the incisor and molar teeth and press the plunger down as far as it will go, depositing the paste on the back of the tongue.

HOW SUPPLIED

Anthelcide EQ paste is supplied in 0.85-oz (24-g) syringes.

STORAGE

Store at controlled room temperature 15°–30°C (59°–86°F).

Approved by FDA under NADA # 121-042
zoetis
Distributed by:
Zoetis Inc.
Kalamazoo, MI 49007
52478000
Revised: November 2025